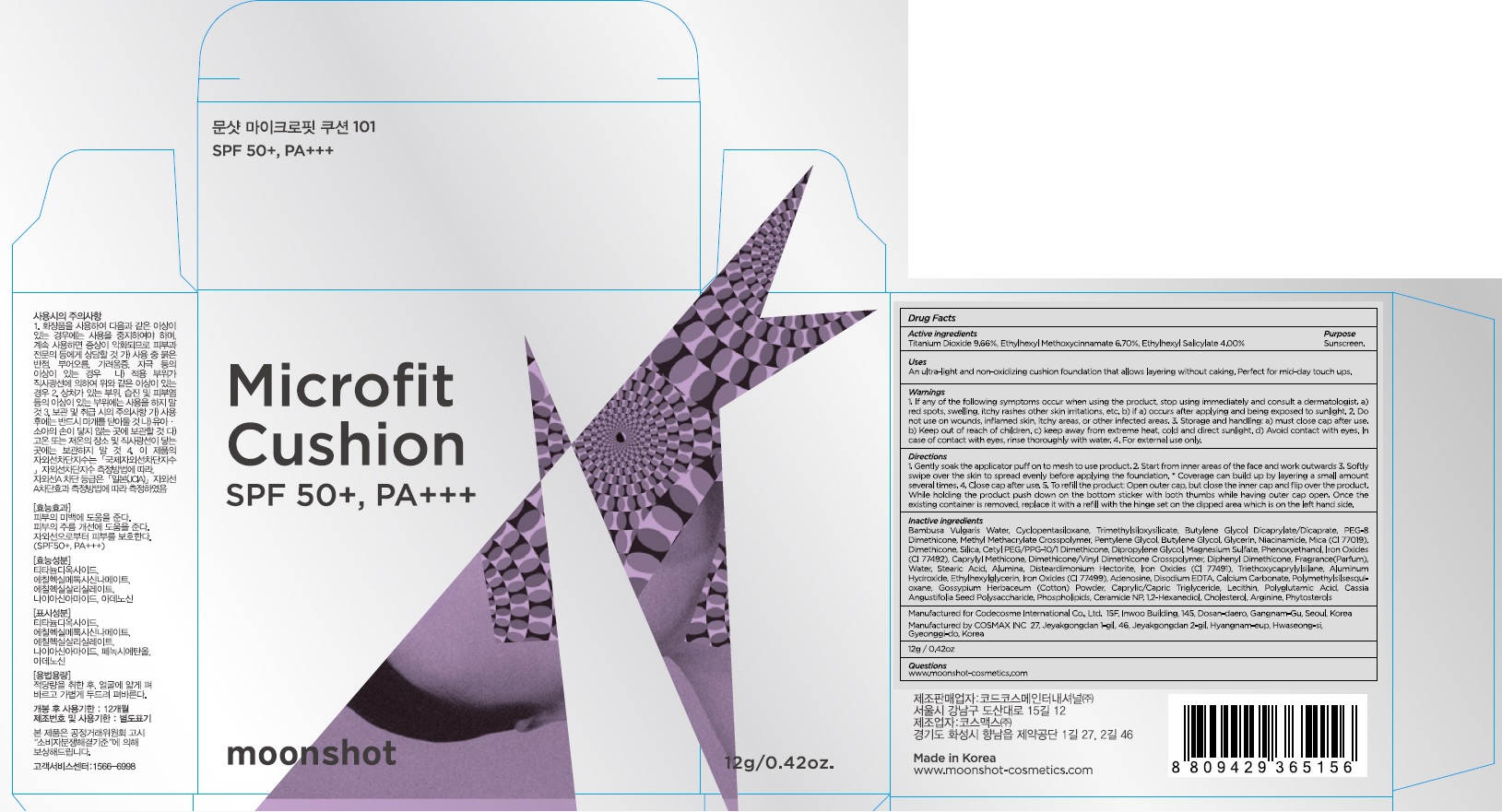 DRUG LABEL: Microfit Cushion 101
NDC: 71786-020 | Form: POWDER
Manufacturer: Codecosme International Co., Ltd.
Category: otc | Type: HUMAN OTC DRUG LABEL
Date: 20171018

ACTIVE INGREDIENTS: Titanium Dioxide 1.15 g/12 g; Octinoxate 0.80 g/12 g; Octisalate 0.48 g/12 g
INACTIVE INGREDIENTS: Butylene Glycol; PEG-8 Dimethicone

ACTIVE INGREDIENT

Active ingredients: Titanium Dioxide 9.66%, Ethylhexyl Methoxycinnamate 6.70%, Ethylhexyl Salicylate 4.00%

INACTIVE INGREDIENT

Inactive ingredients: Bambusa Vulgaris Water, Cyclopentasiloxane, Trimethylsiloxysilicate, Butylene Glycol Dicaprylate/Dicaprate, PEG-8 Dimethicone, Methyl Methacrylate Crosspolymer, Pentylene Glycol, Butylene Glycol, Glycerin, Niacinamide, Mica (CI 77019), Dimethicone, Silica, Cetyl PEG/PPG-10/1 Dimethicone, Dipropylene Glycol, Magnesium Sulfate, Phenoxyethanol, Iron Oxides (CI 77492), Caprylyl Methicone, Dimethicone/Vinyl Dimethicone Crosspolymer, Diphenyl Dimethicone, Fragrance(Parfum), Water, Stearic Acid, Alumina, Disteardimonium Hectorite, Iron Oxides (CI 77491), Triethoxycaprylylsilane, Aluminum Hydroxide, Ethylhexylglycerin, Iron Oxides (CI 77499), Adenosine, Disodium EDTA, Calcium Carbonate, Polymethylsilsesquioxane, Gossypium Herbaceum (Cotton) Powder, Caprylic/Capric Triglyceride, Lecithin, Polyglutamic Acid, Cassia Angustifolia Seed Polysaccharide, Phospholipids, Ceramide NP, 1,2-Hexanediol, Cholesterol, Arginine, Phytosterols

PURPOSE

Purpose: Sunscreen

WARNINGS

Warnings: 1. If any of the following symptoms occur when using the product, stop using immediately and consult a dermatologist. a) red spots, swelling, itchy rashes other skin irritations, etc. b) if a) occurs after applying and being exposed to sunlight. 2. Do not use on wounds, inflamed skin, itchy areas, or other infected areas. 3. Storage and handling: a) must close cap after use. b) Keep out of reach of children. c) keep away from extreme heat, cold and direct sunlight. d) Avoid contact with eyes. In case of contact with eyes, rinse thoroughly with water. 4. For external use only.

DESCRIPTION

Uses: An ultra-light and non-oxidizing cushion foundation that allows layering without caking. Perfect for mid-day touch ups.

Directions: 1. Gently soak the applicator puff on to mesh to use product. 2. Start from inner areas of the face and work outwards 3. Softly swipe over the skin to spread evenly before applying the foundation. * Coverage can build up by layering a small amount several times. 4. Close cap after use. 5. To refill the product: Open outer cap, but close the inner cap and flip over the product. While holding the product push down on the bottom sticker with both thumbs while having outer cap open. Once the existing container is removed, replace it with a refill with the hinge set on the dipped area which is on the left hand side.